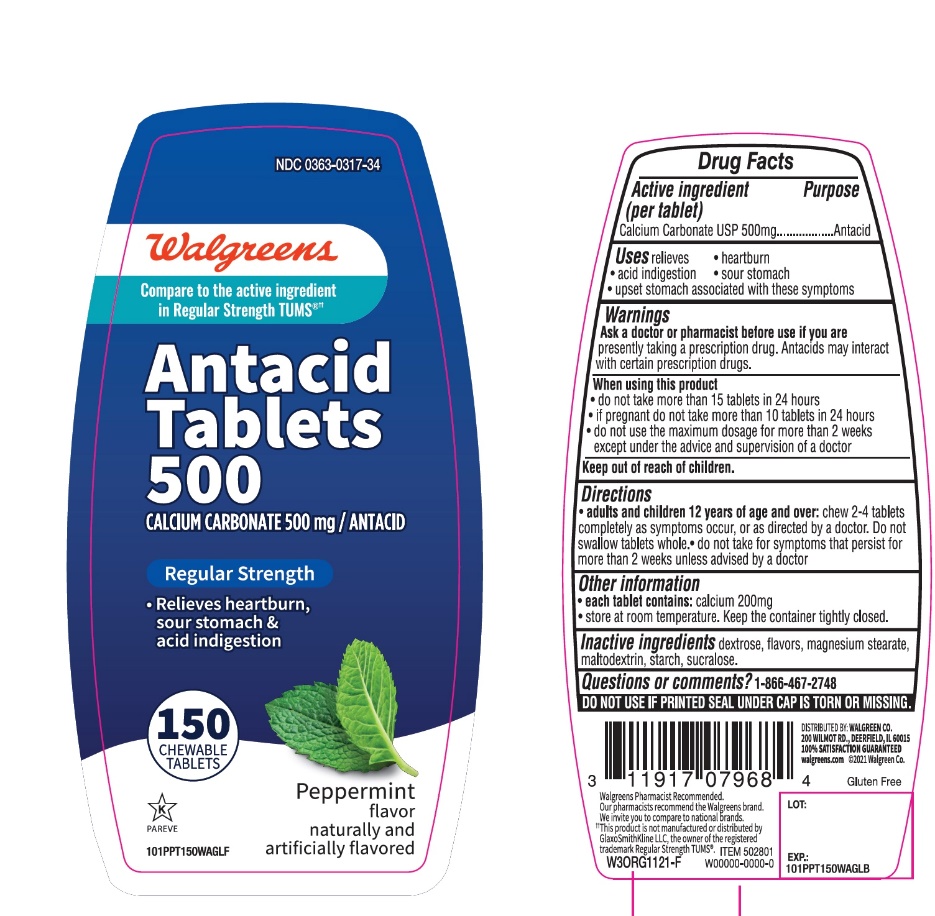 DRUG LABEL: Antacid Regular Strength
NDC: 0363-0317 | Form: TABLET, CHEWABLE
Manufacturer: WALGREEN CO.
Category: otc | Type: HUMAN OTC DRUG LABEL
Date: 20251125

ACTIVE INGREDIENTS: CALCIUM CARBONATE 500 mg/1 1
INACTIVE INGREDIENTS: DEXTROSE, UNSPECIFIED FORM; MAGNESIUM STEARATE; MALTODEXTRIN; STARCH, CORN; SUCRALOSE

Walgreens Antacid Tablets 500 Calcium Carbonate 500 mg Regular Strength peppermint Flavor 150Chewable Tablets

Active ingredient (per tablet)

Calcium Carbonate USP 500mg

Purpose

Antacid

Uses

relieves

• heartburn

• acid indigestion

• sour stomach

• upset stomach associated with these symptoms

Warnings

Ask a doctor or pharmacist before use if you arepresently taking a prescription drug. Antacids may interact with certain prescription drugs.

When using this product

- do not take more than 15 tablets in 24 hours
- if pregnant do not take more than 10 tablets in 24 hours
- do not use the maximum dosage for more than 2 weeks except under the advice and supervision of a doctor.

Directions

- adults and children 12 years of age and over:chew 2-4 tablets completely as symptoms occur, or as directed by a doctor. Do not swallow tablets whole.
- do not take for symptoms that persist for more than 2 weeks unless advised by a doctor

Other information

- each tablet contains:elemental calcium 200mg
- store at room temperature. Keep the container tightly closed.

Inactive ingredients

dextrose, flavors, magnesium stearate, maltodextrin, starch, sucralose.

Questions or comments?

1-866-467-2748

SAFETY SEALED: DO NOT USE IF PRINTED SEAL UNDER CAP IS TORN OR MISSING

Package/Label Principal Display Panel

Walgreens

Compare to TUMS®active ingredient††

NDC 0363-0317-34

Antacid Tablets 500

CALCIUM CARBONATE 500 MG/ANTACID

REGULAR STRENGTH

- Relieves heartburn, sour stomach & acid indigestion

PEPPERMINT FLAVOR

150 CHEWABLE TABLETS

DISTRIBUTED BY: WALGREEN CO.

200 WILMOT RD.,DEERFIELD,IL 60015

100% SATISFACTION GUARANTEED

Walgreens.com ©2017 Walgreen Co

Walgreens Pharmacist Recommended

Walgreens Pharmacist Survey

††This product is not manufactured or distributed by GlaxoSmithKline, the distributor of TUMS®.